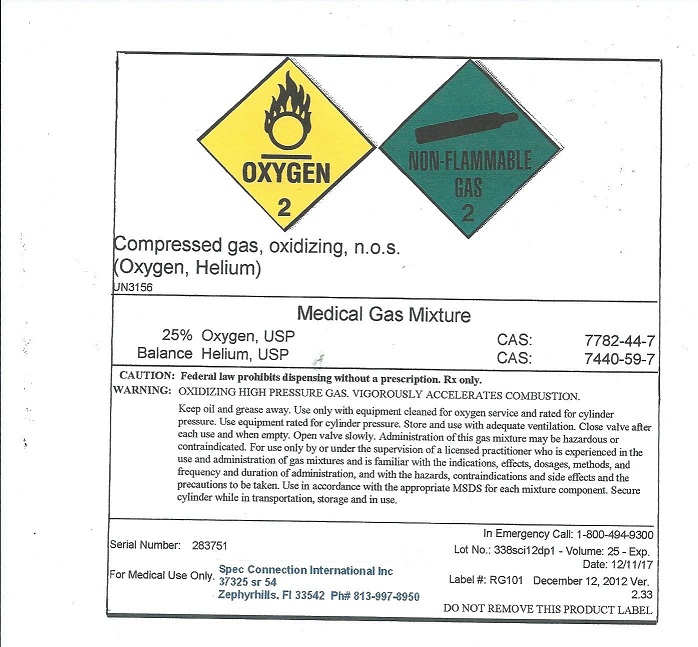 DRUG LABEL: Heliox
NDC: 54776-001 | Form: GAS
Manufacturer: Spec Connection International Inc
Category: prescription | Type: HUMAN PRESCRIPTION DRUG LABEL
Date: 20121219

ACTIVE INGREDIENTS: Oxygen 300 mL/1 L; Helium 700 mL/1 L

Heliox

PACKAGE LABEL

OXYGEN 2 NON-FLAMMABLE GAS 2 Compressed Gas, oxidizing, n.o.s. (Oxygen, Helium) UN3156 Medical Gas Mixture 25% Oxygen, USP CAS: 7782-44-7 Balance Helium, USP CAS: 7740-59-7 CAUTION: Federal law prohibits dispensing without a prescription. Rx Only. WARNING: OXIDIZING HIGH PRESSURE GAS. VIGOROUSLY ACCELERATES COMBUSTION. Keep oil and grease away. Use only with equipment cleaned for oxygen service and rated for cylinder pressure. Use equipment rated for cylinde pressure. Store and use with adequate ventilation. Close valve after each use and when empty. Open valve slowly. Administration of this gas mixture may be hazardous or contraindicated. For use only by or under the supervision of a licensed practitioner who is experienced in the use and administration of gas mixtures and is familiar with the indications, effects, dosages, methods, and frequency and duration of administration, and with the hazards, contraindications and side effects and the precautions to be taken. Use in accordance with the appropriate MSDS for each mixture component. Secure cylinder while in transportation, storage, and in use. Serial Number: 283751 In Emergency Call: 1-800-494-9300 Lot No: 338sci12dp1 Volume 25 Exp Date: 12/11/17 Label #: RG101 December 12, 2012 Ver 2.33 For Medical Use Only. Spec Connection International Inc 37325 sr 54 Zephyrhills, FL 33542 Ph# 813-997-8950